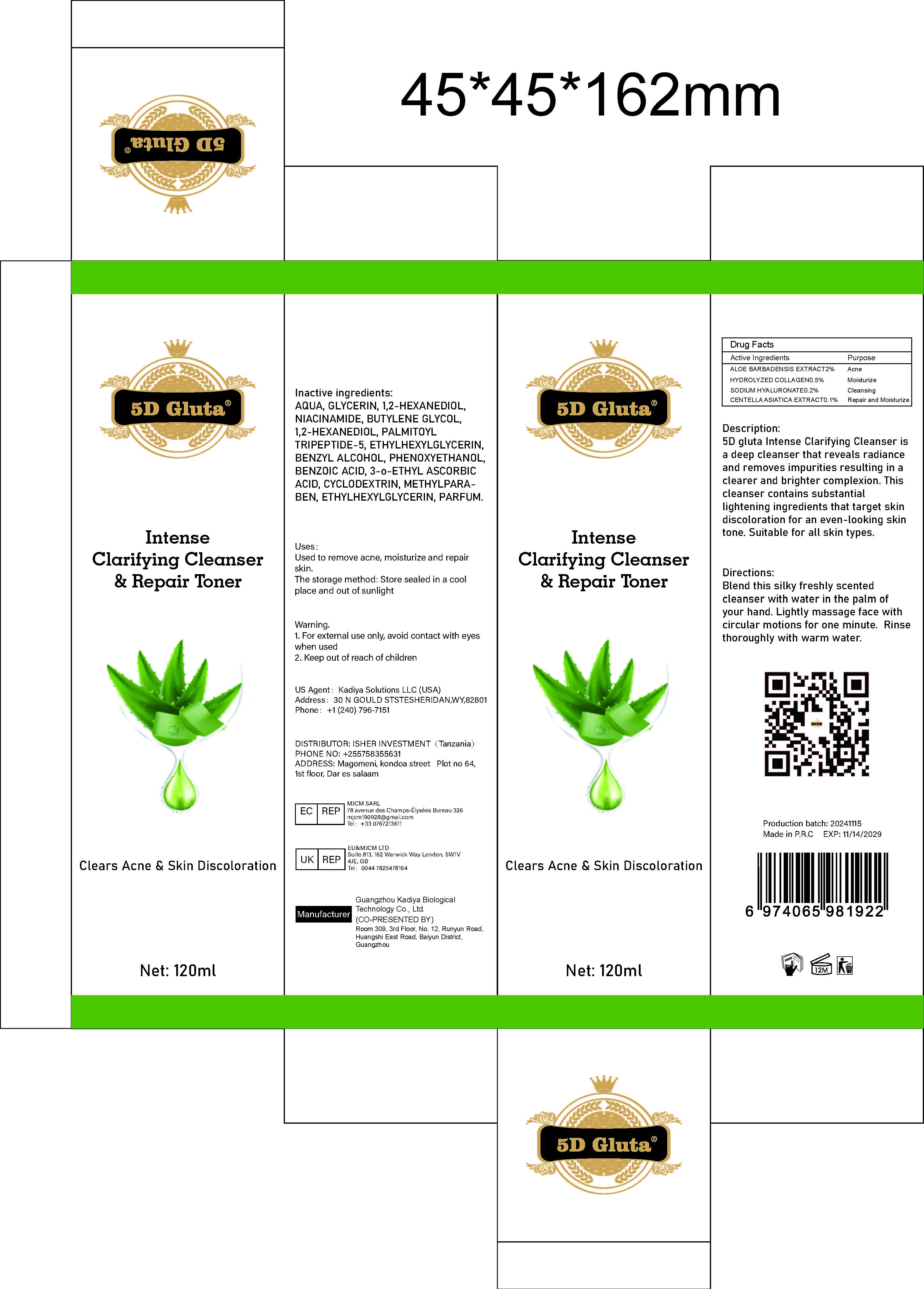 DRUG LABEL: IntenseClarifyingCleanserRepairToner
NDC: 84423-069 | Form: LIQUID
Manufacturer: Guangzhou Kadiya Biotechnology Co., Ltd.
Category: otc | Type: HUMAN OTC DRUG LABEL
Date: 20250217

ACTIVE INGREDIENTS: ALOE VERA WHOLE 2.4 g/120 mL; CENTELLA ASIATICA TRITERPENOIDS 0.12 g/120 mL
INACTIVE INGREDIENTS: BENZOIC ACID; BUTYLENE GLYCOL; CYCLODEXTRIN; ETHYLHEXYLGLYCERIN; AQUA; METHYLPARABEN; SODIUM HYALURONATE; PHENOXYETHANOL; PALMITOYL TRIPEPTIDE-5; BENZYL ALCOHOL; GLYCERIN; NIACINAMIDE; 3-O-ETHYL ASCORBIC ACID; 1,2-HEXANEDIOL

PURPOSE

Used to remove acne, moisturize and repair skin.

INACTIVE INGREDIENT

AQUA，GLYCERIN，1,2-HEXANEDIOL，NIACINAMIDE，BUTYLENE GLYCOL，1,2-HEXANEDIOL，PALMITOYL TRIPEPTIDE-5，ETHYLHEXYLGLYCERIN，BENZYL ALCOHOL，PHENOXYETHANOL，BENZOIC ACID，3-o-ETHYL ASCORBIC ACID，CYCLODEXTRIN，METHYLPARABEN，ETHYLHEXYLGLYCERIN，PARFUM

Warning.
1、For external use only, avoid contact with eyes when used
2、Keep out of reach of children

INDICATIONS AND USAGE

Used to remove acne, moisturize and repair kin

DOSAGE AND ADMINISTRATION

Blend this silky freshly scented cleanser with water in the palm of your hand. Lightly massage face with circular motions for one minute. Rinse thoroughly with warm water.

KEEP OUT OF REACH OF CHILDREN SECTION

Active Ingredients
ALOE BARBADENSIS EXTRACT2%
HYDROLYZED COLLAGEN0.5%
SODIUM HYALURONATE0.2%
CENTELLA ASIATICA EXTRACT0.1%

KEEP OUT OF REACH OF CHILDREN SECTION

PACKAGE LABEL

Active Ingredients
ALOE BARBADENSIS EXTRACT2%
HYDROLYZED COLLAGEN0.5%
SODIUM HYALURONATE0.2%
CENTELLA ASIATICA EXTRACT0.1%

Uses：
Used to remove acne, moisturize and repair skin.
The storage method：
Store sealed in a cool place and out of sunlight

Warning.
1、For external use only, avoid contact with eyes when used
2、Keep out of reach of children

Inactive ingredients：
AQUA，GLYCERIN，1,2-HEXANEDIOL，NIACINAMIDE，BUTYLENE GLYCOL，1,2-HEXANEDIOL，PALMITOYL TRIPEPTIDE-5，ETHYLHEXYLGLYCERIN，BENZYL ALCOHOL，PHENOXYETHANOL，BENZOIC ACID，3-o-ETHYL ASCORBIC ACID，CYCLODEXTRIN，METHYLPARABEN，ETHYLHEXYLGLYCERIN，PARFUM